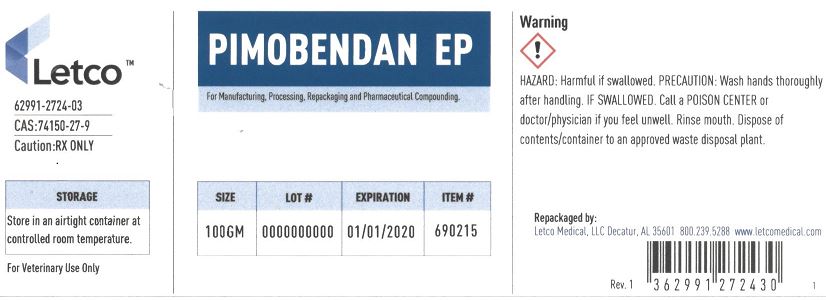 DRUG LABEL: Pimobendan EP5
NDC: 62991-2724 | Form: POWDER
Manufacturer: LETCO MEDICAL, LLC
Category: other | Type: BULK INGREDIENT - ANIMAL DRUG
Date: 20240718

ACTIVE INGREDIENTS: PIMOBENDAN 1 g/1 g

Pimobendan EP5

PACKAGE LABEL

Pimobendan EP 100gm